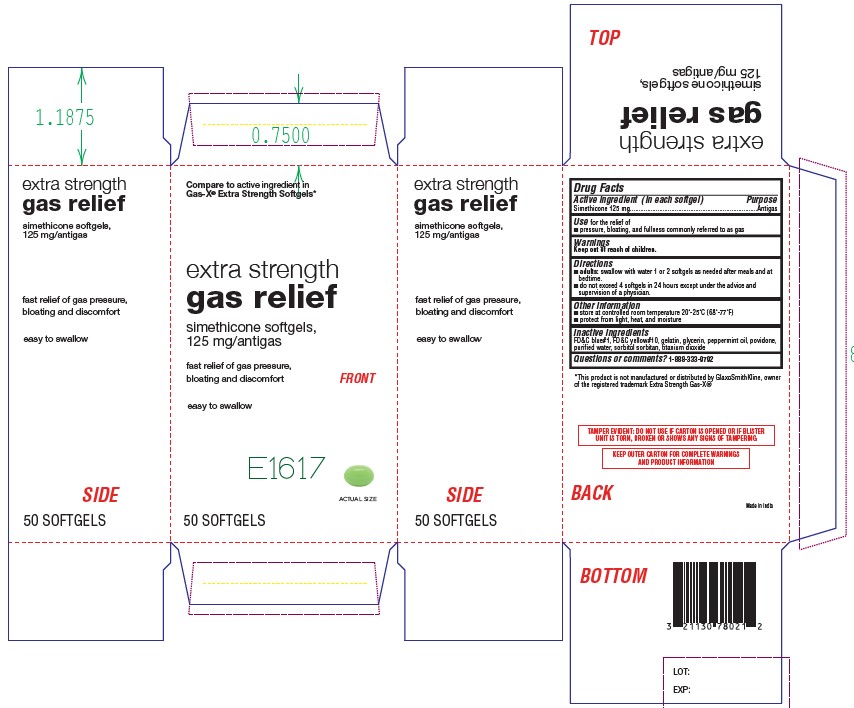 DRUG LABEL: Extra Strength Gas Relief
NDC: 21130-317 | Form: CAPSULE, LIQUID FILLED
Manufacturer: Better Living Brands LLC
Category: otc | Type: HUMAN OTC DRUG LABEL
Date: 20241230

ACTIVE INGREDIENTS: DIMETHICONE 125 mg/1 1
INACTIVE INGREDIENTS: D&C YELLOW NO. 10; GELATIN; GLYCERIN; PEPPERMINT OIL; WATER; SORBITOL; TITANIUM DIOXIDE; FD&C BLUE NO. 1

Extra Strength Gas Relief

Active Ingredient (in each softgel)

Simethicone 125 mg

Purpose

Antigas

Uses

for the relief of • pressure, bloating, and fullness commonly referred to as gas

Warnings

Keep out of reach of children

Directions

• adults: swallow with water 1 or 2 softgels as needed after meals and at bedtime • do not exceed 4 softgels in 24 hours except under the advice and supervision of a physician

Other Information

• store at controlled room temperature 20-25°C (68-77°F)
• protect from light, heat, and moisture

Inactive ingredients

FD&C Blue No. 1, FD&C Yellow No. 10, gelatin, glycerin, peppermint oil, purified water, sorbitol sorbitan, titanium dioxide

Questions or comments?

1-888-333-9792